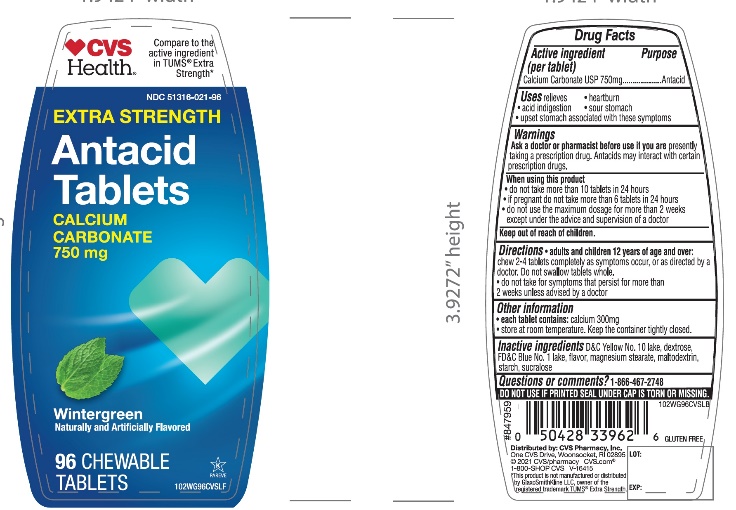 DRUG LABEL: Extra Strength
NDC: 51316-021 | Form: TABLET, CHEWABLE
Manufacturer: CVS PHARMACY
Category: otc | Type: HUMAN OTC DRUG LABEL
Date: 20251204

ACTIVE INGREDIENTS: CALCIUM CARBONATE 750 mg/1 1
INACTIVE INGREDIENTS: D&C YELLOW NO. 10; DEXTROSE, UNSPECIFIED FORM; FD&C BLUE NO. 1; MAGNESIUM STEARATE; MALTODEXTRIN; STARCH, CORN; SUCRALOSE

CVS Extra Strength Antacid Tablets Wintergreen Flavor Drug Facts

Active ingredient (per tablet)

Calcium Carbonate USP 750mg

Purpose

Antacid

Uses

relieves

- heartburn
- sour stomach
- acid indigestion
- upset stomach associated with these symptoms

Warnings

Ask a doctor or pharmacist before use if you are

- presently taking a prescription drug. Antacids may interact with certain prescription drugs.

When using this product

- do not take more than 10 tablets in 24 hours
- if pregnant do not take more than 6 tablets in 24 hours
- do not use the maximum dosage for more than 2 weeks except under the advice and supervision of a doctor

Directions

- adults and children 12 years of age and over:chew 2-4 tablets as symptoms occur, or as directed by a doctor. Do not swallow tablets whole.
- do not take for symptoms that persist for more than 2 weeks unless advised by a doctor

Other information

- each tablet contains:calcium 300mg
- store at room temperature. Keep the container tightly closed

DO NOT USE IF PRINTED SEAL UNDER CAP IS TORN OR MISSING

Inactive ingredients

D&C Yellow No. 10, dextrose, FD&C Blue No. 1, flavor, magnesium stearate, maltodextrin, starch, sucralose

Questions or comments?

1-866-467-2748

Package/Label Principal Display Panel

NDC# 51316-021-96

*Compare to the active ingredient in Extra Strength Tums®

EXTRA STRENGTH

Antacid Tablets

Calcium Carbonate 750 mg

Fast Relief of Upset Stomach, Heartburn and Acid Indigestion

Wintergreen

Naturally and Artificially Flavored

96 Chewable Tablets

GLUTEN FREE

100% Satisfaction Guaranteed!

K PAREVE

Distributed by:

*This product is not manufactured or distributed by GlaxoSmithKline LLC, owner of the registered trademark, Extra Strength Tums®